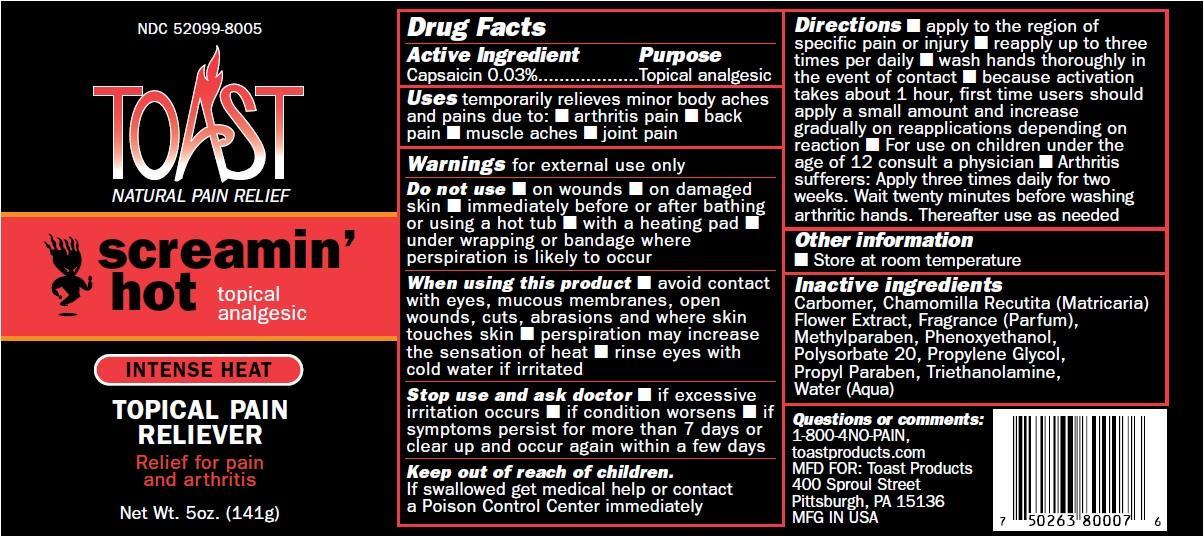 DRUG LABEL: SCREAMIN HOT TOAST
NDC: 52099-8005 | Form: CREAM
Manufacturer: Q.A. Laboratories
Category: otc | Type: HUMAN OTC DRUG LABEL
Date: 20220117

ACTIVE INGREDIENTS: CAPSAICIN 3 g/100 g
INACTIVE INGREDIENTS: CARBOMER HOMOPOLYMER TYPE C (ALLYL PENTAERYTHRITOL CROSSLINKED); CHAMOMILE; DMDM HYDANTOIN; IMIDUREA; METHYLPARABEN; POLYSORBATE 20; PROPYL GALLATE; PROPYLENE GLYCOL; PROPYLPARABEN; TROLAMINE; WATER

Drug Facts

Active Ingredient Purpose
Capsaicin 0.03%...................Topical analgesic

PURPOSE

Uses temporarily relieves minor body aches and pains due to: ar thritis pain, back pain, muscle aches,joint pain.

Warnings for external use only

Do not use immediately before or after bathing or using a hot tub, in conjunction with heating pad,under wrapping or bandage where perspiration is likely to occur.

Stop use and ask doctor if excessive irritation occurs, if condition worsens, if symptoms persist for more than 7 days or clear up and occur again within a few days.

When using this product avoid contact with eyes, mucous membranes, open wounds, cuts, abrasions and where skin touches skin, perspiration may increase the sensation of heat, rinse eyes with cold water if irritated.

Stop use and ask doctor if excessive irritation occurs, if condition worsens ,if symptoms persist for more than 7 days or clear up and occur again within a few days.

Keep out of reach of children. If swallowed get medical help or contact a Poison Control Center immediately

INDICATIONS AND USAGE

Directions apply to the region of specific pain or injury, reapply up to three times per daily, wash hands thoroughly in the event of contact, because activation takes about 1 hour, first time users should apply a small amount and increase gradually on reapplications depending on reaction.For use on children under the age of 12 consult a physician. Arthritis sufferers: Apply three times daily for two weeks. Wait twenty minutes before washing arthritic hands. Thereafter use as needed.

Other information
Store at room temperature

Inactive ingredients
Carbomer, Chamomilla Recutita (Matricaria)
Flower Extract, DMDM Hydantoin, Fragrance
(Par fum), Imidazolidinyl Urea, Methylparaben,
Polysorbate 20, Propyl Gallate,
Propylene Glycol, Propylparaben,
Triethanolamine, Water (Aqua)

Questions or comments:
1-800-4NO-PAIN,
toastproducts.com
MFD FOR: Toast Products
400 Sproul Street,
Pittsburgh, PA 15136
MFG IN USA

DOSAGE AND ADMINISTRATION

apply to the region of specific pain or injury